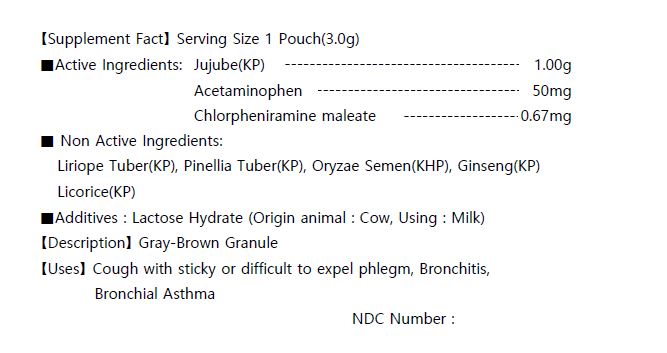 DRUG LABEL: MaekMunDong Tang Extract
NDC: 73442-0011 | Form: GRANULE
Manufacturer: I World Pharmaceutical Co., Ltd.
Category: otc | Type: HUMAN OTC DRUG LABEL
Date: 20200915

ACTIVE INGREDIENTS: JUJUBE FRUIT 1 g/3 g; ACETAMINOPHEN 0.05 g/3 g; CHLORPHENIRAMINE MALEATE 0.00067 g/3 g
INACTIVE INGREDIENTS: LACTOSE MONOHYDRATE

ACTIVE INGREDIENT

Jujube(KP)
Acetaminophen
Chlorpheniramine maleate

PURPOSE

Cough with sticky or difficult to expel phlegm, Bronchitis,

Keep out of reach of children

INDICATIONS AND USAGE

for adults take 1 pouch per intake, 3 times a day, before or between meals

Keep out of reach of children. In case of overdose, get medical help or contact a Poison Control Center right away.

INACTIVE INGREDIENT

Liriope Tuber(KP), Pinellia Tuber(KP), Oryzae Semen(KHP), Ginseng(KP), licorice(KP)

DOSAGE AND ADMINISTRATION

For oral use only